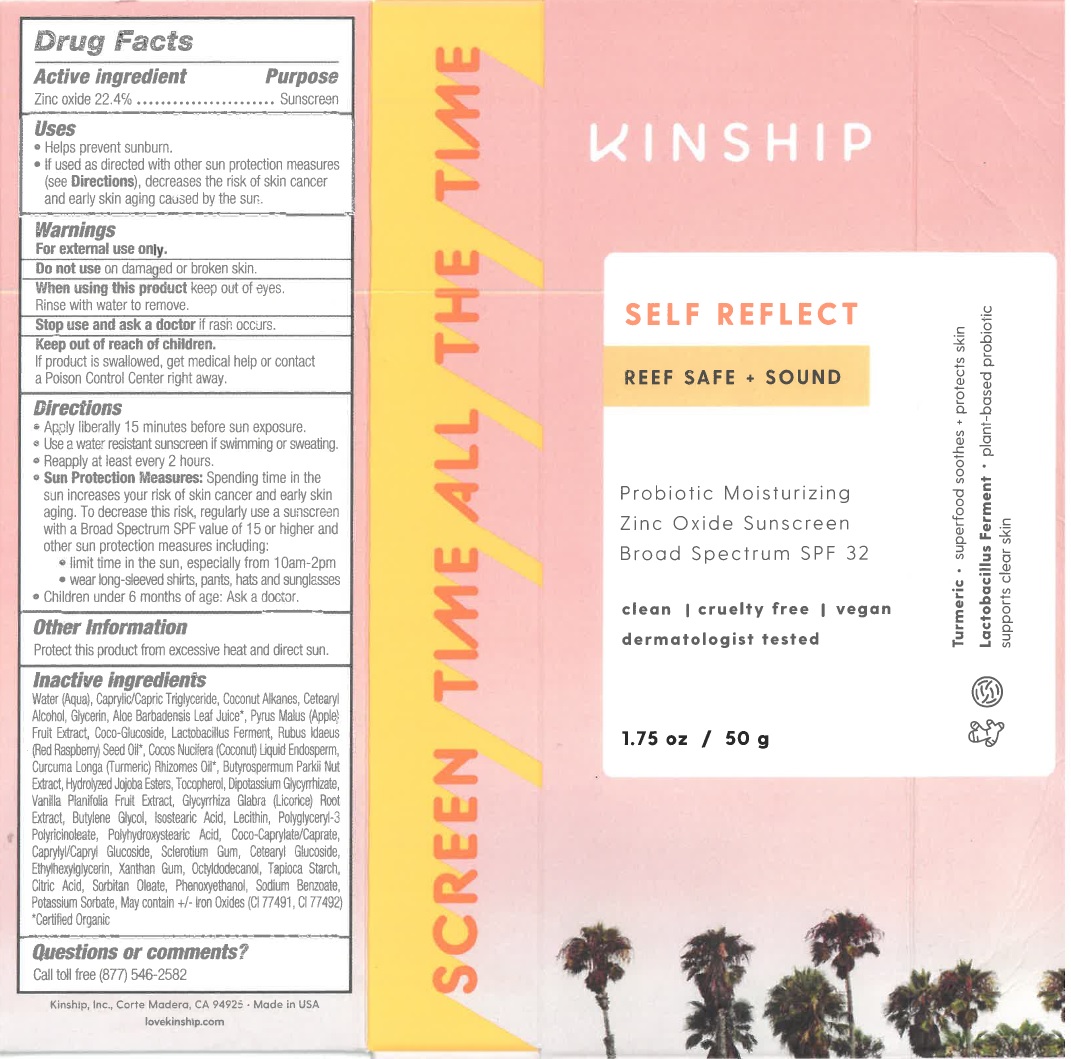 DRUG LABEL: Self Reflect Probiotic Sunscreen Moisturizer Broad Spectrum SPF 32
NDC: 62742-4181 | Form: CREAM
Manufacturer: Allure Labs Inc
Category: otc | Type: HUMAN OTC DRUG LABEL
Date: 20191212

ACTIVE INGREDIENTS: ZINC OXIDE 224 mg/1 g
INACTIVE INGREDIENTS: WATER; MEDIUM-CHAIN TRIGLYCERIDES; COCONUT ALKANES; CETOSTEARYL ALCOHOL; GLYCERIN; ALOE VERA LEAF; APPLE; COCO GLUCOSIDE; LACTOBACILLUS REUTERI; RASPBERRY SEED OIL; COCONUT WATER; TURMERIC OIL; SHEANUT; HYDROLYZED JOJOBA ESTERS (ACID FORM); TOCOPHEROL; GLYCYRRHIZINATE DIPOTASSIUM; VANILLA; GLYCYRRHIZA GLABRA; BUTYLENE GLYCOL; ISOSTEARIC ACID; LECITHIN, SOYBEAN; POLYGLYCERYL-3 RICINOLEATE; POLYHYDROXYSTEARIC ACID (2300 MW); COCO-CAPRYLATE/CAPRATE; CAPRYLYL/CAPRYL OLIGOGLUCOSIDE; BETASIZOFIRAN; CETEARYL GLUCOSIDE; ETHYLHEXYLGLYCERIN; XANTHAN GUM; OCTYLDODECANOL; STARCH, TAPIOCA; CITRIC ACID MONOHYDRATE; SORBITAN MONOOLEATE; PHENOXYETHANOL; SODIUM BENZOATE; POTASSIUM SORBATE; FERRIC OXIDE RED; FERRIC OXIDE YELLOW

DRUG FACTS

Active Ingredients:

Zinc Oxide 22.4%

Purpose: Sunscreen

Uses:

- Helps prevent sunburn.
- If used as directed with other sun protection measures (see Direction), decreases the risk of skin cancer and early skin aging caused by the sun.

WARNINGS AND PRECAUTIONS

Warning: For external use only.

Do not use: on damaged or broken skin.

When using this products:

- Keep out of eyes.
- Rinse with water to remove.

Stop use and ask a doctor: If rash occurs.

Keep out of reach of children:

- If product is swallowed, get medical help or contact a Poison Control Center right away.

Directions:

- Apply generously 15 minutes before sun exposer.
- Use a water resistant sunscreen if swimming or sweating.
- Reapply at least every 2 hours.
- Sun protection measures: Spending time in the sun increase your risk of skin cancer and early skin aging. To decrease this risk, regularly use a sunscreen with a Broad Spectrum SPF of 15 or higher and other sun protection measures including:
- Limit time in the sun, especially from 10am - 2pm.
- Wear long sleeved shirts, pants, hats and sunglasses.
- Children under 6 months: Ask a doctor.

Other Information: Protect the product from excessive heat and direct sun.

INACTIVE INGREDIENT

Inactive Ingredients: Water (Aqua), Caprylyc/Capric Triglyceride, Coconut Alkanes, Cetearyl Alcohol, Glycerin, Aloe Barbadensis Leaf Juice, Pyrus Malus (Apple) Fruit Extract, Coco-Glucoside, Lactobacillus Ferment, Rubus Idaeus (Red Rasberry) Seed Oil, Cocos Nucifera (Coconut) Liquid Endosperm, Curcuma Longa (Turmeric) Rhizomes Oil, Butyrospermum Parkii Nut Extract, Hydrolyzed Jojoba Esters, Tocopherol, Dipotassium Glycyrrhizate, Vanilla Planifolia Fruit Extract, Glycyrrhiza Glabra (Licorice) Root Extract, Butylene Glycol, Isostearic Acid, Lecithin, Polyglyceryl-3 Polyricinoleate, Polyhydroxystearic Acid, Coco-Caprylate/Caprate, Caprylyl/Capryl Glucoside, Sclerotium Gum, Cetearyl Glucoside, Ethylhexylglycerin, Xanthan Gum, Octyldodecanol, Tapioca Starch, Citric Acid, Sorbitan Oleate, Phenoxyethanol, Sodium Benzoate, Potassium Sorbate, May contains +/- Iron Oxides (Cl77491, Cl77492)

Questions or Comments?

Call toll free (877) 456-2582

PACKAGE LABEL

Kinship Inc.,

Corte Modera, CA 94925

Made in USA

lovekinship.com